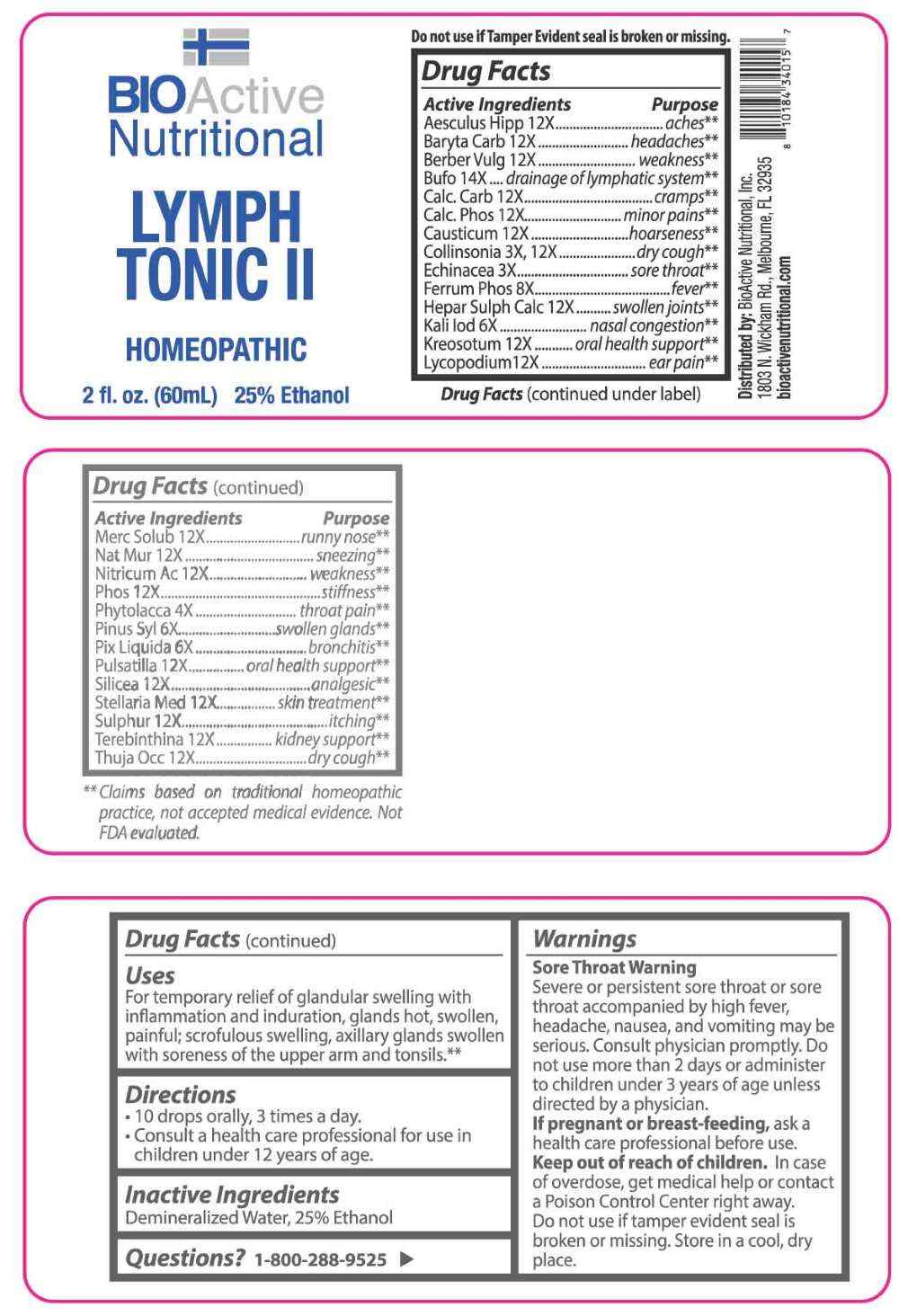 DRUG LABEL: Lymph Tonic II
NDC: 43857-0658 | Form: LIQUID
Manufacturer: BioActive Nutritional, Inc.
Category: homeopathic | Type: HUMAN OTC DRUG LABEL
Date: 20251229

ACTIVE INGREDIENTS: ECHINACEA ANGUSTIFOLIA WHOLE 3 [hp_X]/1 mL; COLLINSONIA CANADENSIS ROOT 3 [hp_X]/1 mL; PHYTOLACCA AMERICANA ROOT 4 [hp_X]/1 mL; POTASSIUM IODIDE 6 [hp_X]/1 mL; PINUS SYLVESTRIS LEAFY TWIG 6 [hp_X]/1 mL; PINE TAR 6 [hp_X]/1 mL; FERROSOFERRIC PHOSPHATE 8 [hp_X]/1 mL; HORSE CHESTNUT 12 [hp_X]/1 mL; BARIUM CARBONATE 12 [hp_X]/1 mL; BERBERIS VULGARIS ROOT BARK 12 [hp_X]/1 mL; OYSTER SHELL CALCIUM CARBONATE, CRUDE 12 [hp_X]/1 mL; TRIBASIC CALCIUM PHOSPHATE 12 [hp_X]/1 mL; CAUSTICUM 12 [hp_X]/1 mL; CALCIUM SULFIDE 12 [hp_X]/1 mL; WOOD CREOSOTE 12 [hp_X]/1 mL; LYCOPODIUM CLAVATUM SPORE 12 [hp_X]/1 mL; MERCURIUS SOLUBILIS 12 [hp_X]/1 mL; SODIUM CHLORIDE 12 [hp_X]/1 mL; NITRIC ACID 12 [hp_X]/1 mL; PHOSPHORUS 12 [hp_X]/1 mL; PULSATILLA PRATENSIS WHOLE 12 [hp_X]/1 mL; SILICON DIOXIDE 12 [hp_X]/1 mL; STELLARIA MEDIA 12 [hp_X]/1 mL; SULFUR 12 [hp_X]/1 mL; TURPENTINE OIL 12 [hp_X]/1 mL; THUJA OCCIDENTALIS LEAFY TWIG 12 [hp_X]/1 mL; BUFO BUFO CUTANEOUS GLAND 14 [hp_X]/1 mL
INACTIVE INGREDIENTS: WATER; ALCOHOL

DRUG FACTS:

ACTIVE INGREDIENTS:

Aesculus Hippocastanum 12X, Baryta Carbonica 12X, Berberis Vulgaris 12X, Bufo Rana 14X, Calcarea Carbonica 12X, Calcarea Phosphorica 12X, Causticum 12X, Collinsonia Canadensis 3X, 12X, Echinacea 3X, Ferrum Phosphoricum 8X, Hepar Sulphuris Calcareum 12X, Kali Iodatum 6X, Kreosotum 12X, Lycopodium Clavatum 12X, Mercurius Solubilis 12X, Natrum Muriaticum 12, Nitricum Acidum 12, Phosphorus 12, Phytolacca Decandra 4X, Pinus Sylvestris 6X, Pix Liquida 6X, Pulsatilla 12X, Silicea 12X, Stellaria Media 12X, Sulphur 12X, Terebinthina 12X, Thuja Occidentalis 12X.

PURPOSE:

Aesculus Hippocastanum - aches,** Baryta Carbonica - headaches,** Berberis Vulgaris - weakness,** Bufo Rana – drainage of lymphatic system,** Calcarea Carbonica - cramps,** Calcarea Phosphorica – minor pains,** Causticum - hoarseness,** Collinsonia Canadensis – dry cough,** Echinacea – sore throat,** Ferrum Phosphoricum - fever,** Hepar Sulphuris Calcareum – swollen joints,** Kali Iodatum – nasal congestion,** Kreosotum – oral health support,** Lycopodium Clavatum – ear pain,** Mercurius Solubilis – runny nose,** Natrum Muriaticum - sneezing,** Nitricum Acidum - weakness,** Phosphorus - stiffness,** Phytolacca Decandra – throat pain,** Pinus Sylvestris – swollen glands,** Pix Liquida - bronchitis,** Pulsatilla – oral health support,** Silicea - analgesic,** Stellaria Media – skin treatment,** Sulphur - itching,** Terebinthina – kidney support,** Thuja Occidentalis – dry cough**

**Claims based on traditional homeopathic practice, not accepted medical evidence. Not FDA evaluated.

INDICATIONS:

For temporary relief of glandular swelling with inflammation and induration, glands hot, swollen, painful; scrofulous swelling, axillary glands swollen with soreness of the upper arm and tonsils.**

**Claims based on traditional homeopathic practice, not accepted medical evidence. Not FDA evaluated.

WARNINGS:

Sore Throat Warning

Severe or persistent sore throat or sore throat accompanied by high fever, headache, nausea, and vomiting may be serious. Consult physician promptly. Do not use more than 2 days or administer to children under 3 years of age unless directed by a physician.

If pregnant or breast-feeding, ask a health care professional before use.

Keep out of reach of children. In case of overdose, get medical help or contact a Poison Control Center right away.

Do not use if tamper evident seal is broken or missing.

Store in a cool, dry place.

KEEP OUT OF REACH OF CHILDREN:

In case of overdose, get medical help or contact a Poison Control Center right away.

DIRECTIONS:

• 10 drops orally, 3 times a day.

• Consult a health care professional for use in children under 12 years of age.

INACTIVE INGREDIENTS:

Demineralized Water, 25% Ethanol

QUESTIONS:

Distributed by:
BioActive Nutritional, Inc.
1803 N. Wickham Rd.
Melbourne, FL 32935
bioactivenutritional.com

1-800-288-9525

PACKAGE LABEL DISPLAY:

BIOActive Nutritional

LYMPH TONIC II

HOMEOPATHIC

2 fl. oz. (60 ml)